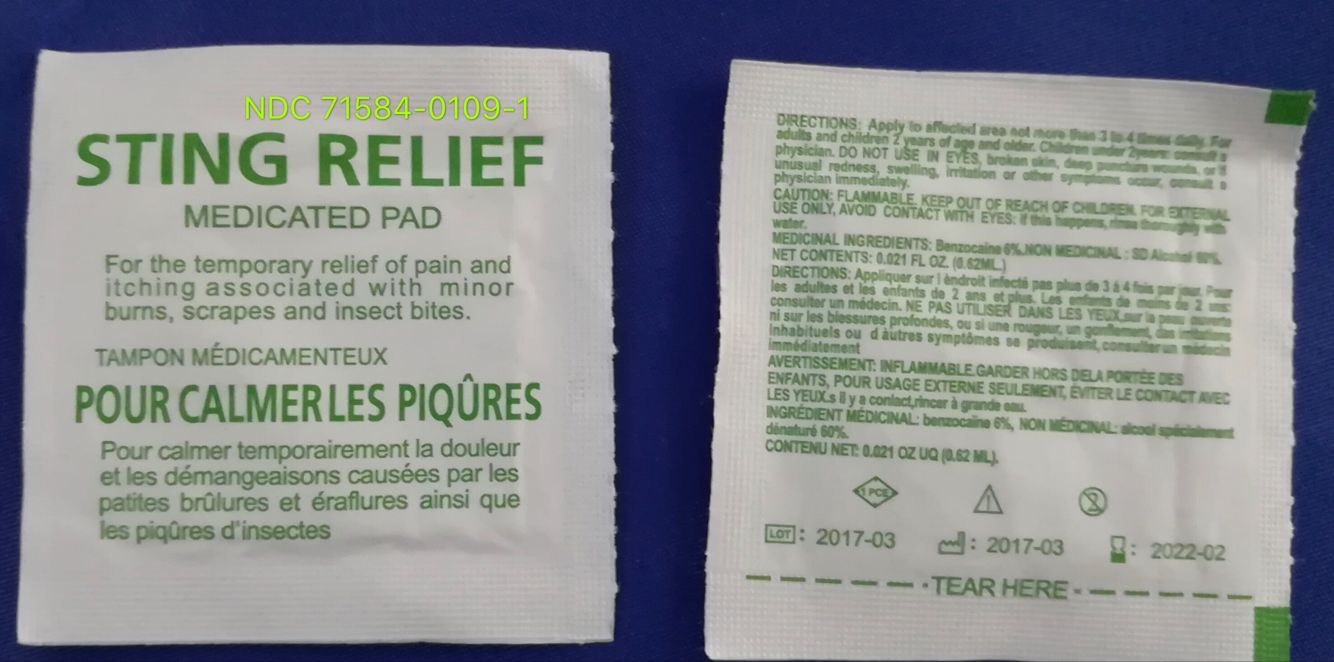 DRUG LABEL: Sting relief pad
NDC: 71584-0109 | Form: SWAB
Manufacturer: Guangdong Comfort Medical Products Co., Ltd.
Category: otc | Type: HUMAN OTC DRUG LABEL
Date: 20251019

ACTIVE INGREDIENTS: BENZOCAINE 6 g/100 mL; ALCOHOL 60 mL/100 mL
INACTIVE INGREDIENTS: WATER

Active Ingredient

Active Ingredient: Purpose:

Benzocaine, 6% w/v.................. Topical Anesthetic

SD alcohol, 60% w/v.................. Antiseptic

Purpose

Topical Anesthetic
Antiseptic

Uses

Use: For the temporary relief of pain and itching associated with minor burns, scrapes and insect bites.

Directions

Clean intended area thoroughly with pad. Discard after single use.

Warnings

Warnings: For external use only.

Avoid contact with eyes. If this happens, rinse thoroughly with water.

Keep out of reach of children

If swallowed, get medical help or contact a Poison Control Center right away.

Inactive Ingredients

Purified water

STORAGE AND HANDLING

Flammable - keep away from fire or flame.

Do not use: In eyes, on broken skin, deep puncture wounds. If unusual redness, swelling, irritation or other symptoms occur, consult a physician immediately.